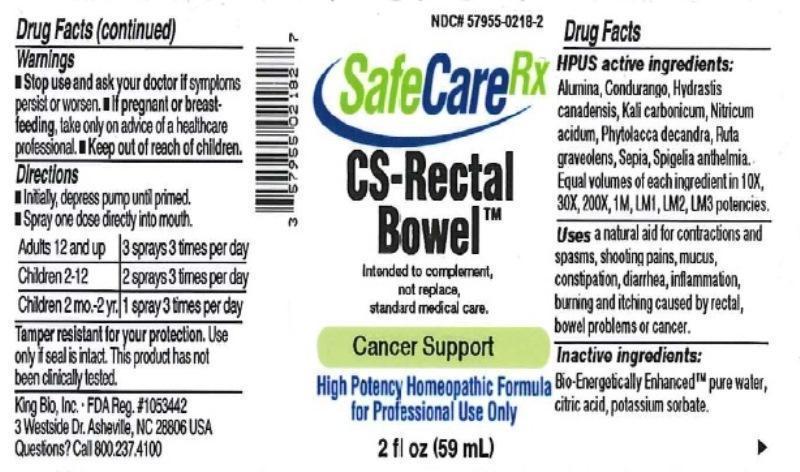 DRUG LABEL: CS Rectal Bowel
NDC: 57955-0218 | Form: LIQUID
Manufacturer: King Bio Inc.
Category: homeopathic | Type: HUMAN OTC DRUG LABEL
Date: 20150829

ACTIVE INGREDIENTS: ALUMINUM OXIDE 10 [hp_X]/59 mL; MARSDENIA CONDURANGO BARK 10 [hp_X]/59 mL; GOLDENSEAL 10 [hp_X]/59 mL; POTASSIUM CARBONATE 10 [hp_X]/59 mL; NITRIC ACID 10 [hp_X]/59 mL; PHYTOLACCA AMERICANA ROOT 10 [hp_X]/59 mL; RUTA GRAVEOLENS FLOWERING TOP 10 [hp_X]/59 mL; SEPIA OFFICINALIS JUICE 10 [hp_X]/59 mL; SPIGELIA ANTHELMIA 10 [hp_X]/59 mL
INACTIVE INGREDIENTS: WATER; ANHYDROUS CITRIC ACID; POTASSIUM SORBATE

CS-Rectal Bowel™

ACTIVE INGREDIENT

Drug Facts__________________________________________________________________________________________________________

HPUS active ingredients: Alumina, Condurango, Hydrastis canadensis, Kali carbonicum, Nitricum acidum, Phytolacca decandra, Ruta graveolens, Sepia, Spigelia anthelmia. Equal volumes of each ingredient in 10X, 30X, 200X, 1M, LM1, LM2, LM3 potencies.

INDICATIONS AND USAGE

Uses a natural aid for contractions and spasms, shooting pains, mucus, constipation, diarrhea, inflammation, burning and itching caused by rectal, bowel problems or cancer.

Inactive Ingredients:

Bio-Energetically Enhanced™ pure water, citric acid and potassium sorbate.

Warnings

- Stop use and ask your doctor if symptoms persist or worsen.
- If pregnant or breast-feeding, take only on advice of a healthcare professional.

- Keep out of reach of children.

Directions

- Initially, depress pump until primed.
- Spray one dose directly into mouth.
- Adults 12 and up: 3 sprays 3 times per day.
- Children 2-12: 2 sprays 3 times per day.
- Children 2 mo-2yr: 1 spray 3 times per day.

OTHER SAFETY INFORMATION

Tamper resistant for your protection. Use only if seal is intact. This product has not been clinically tested.

PURPOSE

Uses a natural aid for:

- contractions and spasms
- shooting pains
- mucus
- constipation
- diarrhea
- inflammation
- burning and itching caused by rectal
- bowel problems
- cancer